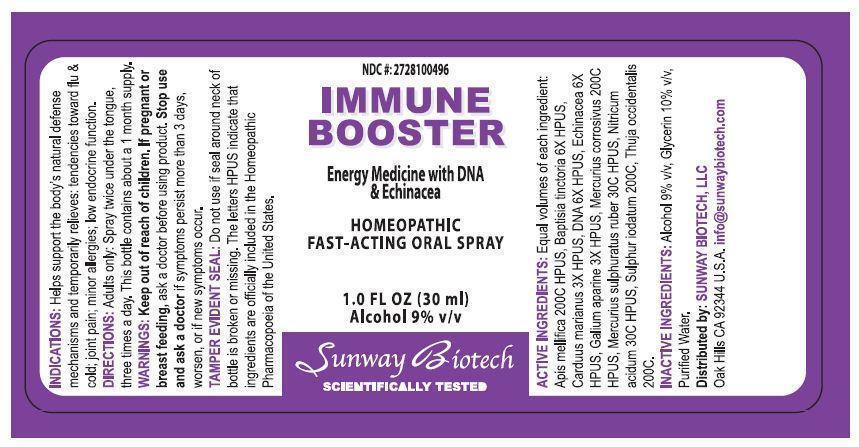 DRUG LABEL: Immune Booster
NDC: 27281-004 | Form: SPRAY
Manufacturer: Sunway Biotech LLC
Category: homeopathic | Type: HUMAN OTC DRUG LABEL
Date: 20131205

ACTIVE INGREDIENTS: APIS MELLIFERA 200 [hp_C]/30 mL; BAPTISIA TINCTORIA 3 [hp_C]/30 mL; SILYBUM MARIANUM SEED OIL 1.5 [hp_C]/30 mL; HERRING SPERM DNA 3 [hp_C]/30 mL; ECHINACEA, UNSPECIFIED 3 [hp_C]/30 mL; GALIUM APARINE 1.5 [hp_C]/30 mL; MERCURIC CHLORIDE 200 [hp_C]/30 mL; MERCURIC SULFIDE 30 [hp_C]/30 mL; NITRIC ACID 30 [hp_C]/30 mL; SULFUR IODIDE 200 [hp_C]/30 mL; THUJA OCCIDENTALIS LEAFY TWIG 200 [hp_C]/30 mL
INACTIVE INGREDIENTS: ALCOHOL; GLYCERIN; WATER

ACTIVE INGREDIENT

Active Ingredients: Equal volumes of each ingredient: Apis Mellifica 200C HPUS, Baptisia Tinctoria 6X HPUS, Carduus Marianus 3X HPUS, DNA 6X HPUS, Echinacea 6X HPUS, Galium Aparine 3X HPUS, Mercurius Corrosivus 200C HPUS, Mercurius Sulphuratus Ruber 30C HPUS, Nitricum Acidum 30C HPUS, Sulphur Iodatum 200C, Thuja Occidentalis 200C.

Keep out of reach of children.

PURPOSE

NDC #: 2728100496

IMMUNE BOOSTER

Energy Medicine with DNA & Echinacea

Homeopathic Fast-Acting Oral Spray

1.0 Fl Oz (30 ml)

Alcohol 9% v/v

INDICATIONS AND USAGE

Indications: Helps support the body's natural defense mechanisms and temporarily relieves: tendencies toward flu & cold; joint pain; minor allergies; low endocrine function.

DOSAGE AND ADMINISTRATION

Directions: Adults only: Spray twice under the tongue, three times a day. This bottle contains about a 1 month supply.

WARNINGS

Warnings: keep out of reach of children. If pregnant or breast feeding, ask a doctor before using product. Stop use and ask a doctor if symptoms persist more than 3 days, worsen, or if new symptoms occur.

OTHER SAFETY INFORMATION

Tamper Evident Seal: Do not use if seal around neck of bottle is broken or missing. The letters HPUS indicate that ingredients are officially included in the Homeopathic Pharmarcopoeia of the United States.

INACTIVE INGREDIENT

Inactive Ingredients: Alcohol 9% v/v, Glycerin 10% v/v, Purified Water.